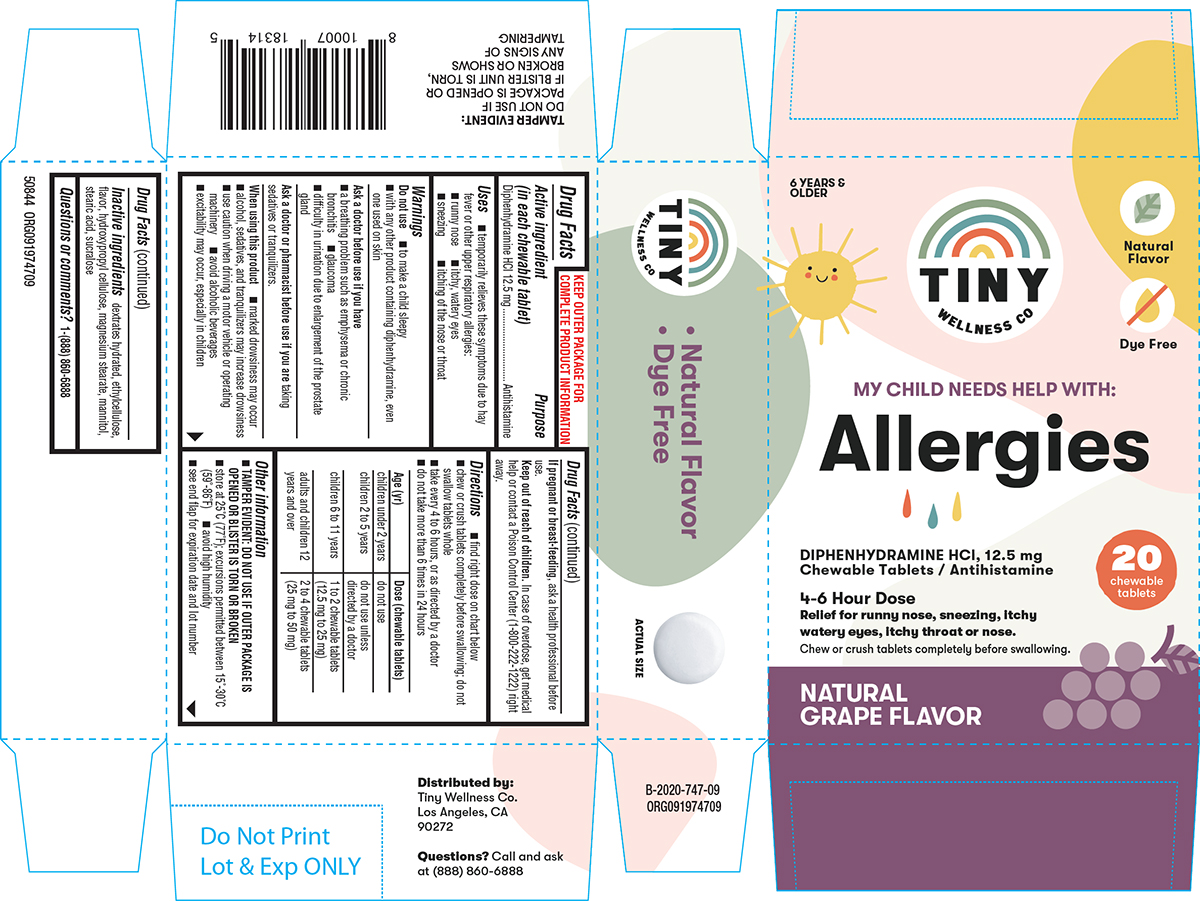 DRUG LABEL: Allergies
NDC: 73418-747 | Form: TABLET, CHEWABLE
Manufacturer: Unconditional Love
Category: otc | Type: HUMAN OTC DRUG LABEL
Date: 20251027

ACTIVE INGREDIENTS: DIPHENHYDRAMINE HYDROCHLORIDE 12.5 mg/1 1
INACTIVE INGREDIENTS: DEXTROSE MONOHYDRATE; ETHYLCELLULOSE, UNSPECIFIED; HYDROXYPROPYL CELLULOSE, UNSPECIFIED; MAGNESIUM STEARATE; MANNITOL; STEARIC ACID; SUCRALOSE

Tiny Wellness 44-747

Active ingredient (in each chewable tablet)

Diphenhydramine HCl 12.5 mg

Purpose

Antihistamine

Uses

- temporarily relieves these symptoms due to hay fever or other upper respiratory allergies:
  - runny nose
  - itchy, watery eyes
  - sneezing
  - itching of the nose or throat

Warnings

Do not use

- to make a child sleepy
- with any other product containing diphenhydramine, even one used on skin

Ask a doctor before use if you have

- a breathing problem such as emphysema or chronic bronchitis
- glaucoma
- difficulty in urination due to enlargement of the prostate gland

Ask a doctor or pharmacist before use if you are

taking sedatives or tranquilizers.

When using this product

- marked drowsiness may occur
- alcohol, sedatives, and tranquilizers may increase drowsiness
- use caution when driving a motor vehicle or operating machinery
- avoid alcoholic beverages
- excitability may occur, especially in children

If pregnant or breast-feeding,

ask a health professional before use.

Keep out of reach of children.

In case of overdose, get medical help or contact a Poison Control Center (1-800-222-1222) right away.

Directions

- find right dose on chart below
- chew or crush tablets completely before swallowing; do not swallow tablets whole
- take every 4 to 6 hours, or as directed by a doctor
- do not take more than 6 times in 24 hours

Age (yr) | Dose (chewable tablets)
children under 2 years | do not use
children 2 to 5 years | do not use unless directed by a doctor
children 6 to 11 years | 1 to 2 chewable tablets (12.5 mg to 25 mg)
adults and children 12 years and over | 2 to 4 chewable tablets (25 mg to 50 mg)

Other information

- TAMPER EVIDENT: DO NOT USE IF OUTER PACKAGE IS OPENED OR BLISTER IS TORN OR BROKEN
- store at 25°C (77°F); excursions permitted between 15°-30°C (59°-86°F)
- avoid high humidity
- see end flap for expiration date and lot number

Inactive ingredients

dextrates hydrated, ethylcellulose, flavor, hydroxypropyl cellulose, magnesium stearate, mannitol, stearic acid, sucralose

Questions or comments?

1-(888) 860-6888

Principal display panel

TINY
WELLNESS CO

6 YEARS &
OLDER

Natural
Flavor

Dye Free

MY CHILD NEEDS HELP WITH:
Allergies

DIPHENHYDRAMINE HCl, 12.5 mg
Chewable Tablets / Antihistamine

4-6 Hour Dose

Relief for runny nose, sneezing, itchy
watery eyes, itchy throat or nose.

Chew or crush tablets completely before swallowing.

20
chewable
tablets

NATURAL
GRAPE FLAVOR

TAMPER EVIDENT:
DO NOT USE IF
PACKAGE IS OPENED OR
IF BLISTER UNIT IS TORN,
BROKEN OR SHOWS
ANY SIGNS OF
TAMPERING

Distributed by:
Tiny Wellness Co.
Los Angeles, CA
90272

Questions? Call and ask
at (888) 860-6888

50844 ORG091974709

Tiny Wellness 44-747